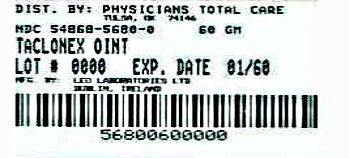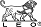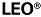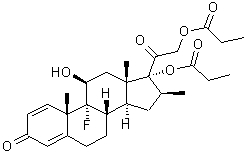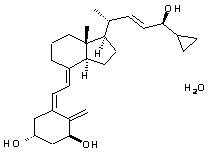 DRUG LABEL: Taclonex
                        
NDC: 54868-5680 | Form: OINTMENT
Manufacturer: Physicians Total Care, Inc.
Category: prescription | Type: HUMAN PRESCRIPTION DRUG LABEL
Date: 20120529

ACTIVE INGREDIENTS: CALCIPOTRIENE HYDRATE 50 ug/1 g; BETAMETHASONE DIPROPIONATE 0.5 mg/1 g
INACTIVE INGREDIENTS: ALPHA-TOCOPHEROL, DL-; MINERAL OIL; PETROLATUM

HIGHLIGHTS OF PRESCRIBING INFORMATION

These highlights do not include all the information needed to use Taclonex® Ointment safely and effectively. See Full Prescribing Information for Taclonex® Ointment.
Taclonex® (calcipotriene 0.005% and betamethasone dipropionate 0.064%) Ointment
For topical use only
Initial U.S. Approval: 2006.

1 INDICATIONS AND USAGE

Taclonex® Ointment is a vitamin D analogue and corticosteroid combination product indicated for the topical treatment of psoriasis vulgaris in adults 18 years of age and older (1.1).

Limitations of Use:

• Do not use on face, axillae or groin (1.2)

• Do not use if skin atrophy is present at the treatment site (1.2)

2 DOSAGE AND ADMINISTRATION

Apply Taclonex® Ointment to affected area(s) once daily for up to 4 weeks. The maximum weekly dose should not exceed 100 g. Treatment of more than 30% body surface area is not recommended (2.1).

Taclonex® Ointment is not for oral, ophthalmic, or intravaginal use.

3 DOSAGE FORMS AND STRENGTHS

Ointment. Soft white (off-white to yellow) paraffin based ointment with calcipotriene 0.005% and betamethasone dipropionate 0.064% (3).

4 CONTRAINDICATIONS

None (4).

5 WARNINGS AND PRECAUTIONS

- Hypercalcemia and hypercalciuria have been reported. If it occurs, discontinue treatment until parameters of calcium metabolism normalize (5.1)
- Topical corticosteroids can produce reversible hypothalamic-pituitary-adrenal (HPA) axis suppression, Cushing's syndrome and unmask latent diabetes (5.2)
- Systemic absorption may require evaluation for HPA axis suppression (5.2)
- Modify use should HPA axis suppression develop (5.2)
- Potent corticosteroids, use on large areas, prolonged use or occlusive use may increase systemic absorption (5.3)
- Local adverse reactions with topical steroids may include atrophy, striae, irritation, acneiform eruptions, hypopigmentation and allergic contact dermatitis and may be more likely with occlusive use or more potent corticosteroids (5.3, 6.1)
- Children may be more susceptible to systemic toxicity when treated with topical corticosteroids (5.2, 8.4)

6 ADVERSE REACTIONS

The most common adverse reactions (≥ 1%) are pruritus and scaly rash.

To report SUSPECTED ADVERSE REACTIONS, contact LEO Pharma Inc. at 1-877-494-4536 or FDA at 1-800-FDA-1088 or www.fda.gov/medwatch.

RECENT MAJOR CHANGES

Warnings and Precautions, Hypercalciuria (5.1)

FULL PRESCRIBING INFORMATION

1 INDICATIONS AND USAGE

1.1 Indication

Taclonex® (calcipotriene and betamethasone dipropionate) Ointment is indicated for the topical treatment of psoriasis vulgaris in adults 18 years of age and older for up to 4 weeks.

1.2 Limitations of Use

- Taclonex® Ointment should not be applied to the face, axillae or groin.
- Taclonex® Ointment should not be used if there is skin atrophy at the treatment site.

2 DOSAGE AND ADMINISTRATION

2.1 Usual Dosage and Administration

Apply an adequate layer of Taclonex® Ointment to the affected area(s) once daily for up to 4 weeks. The maximum weekly dose should not exceed 100 g. Treatment of more than 30% body surface area is not recommended. Taclonex® Ointment should be rubbed in gently and completely. Patients should wash their hands after applying Taclonex® Ointment.

Taclonex® Ointment is not for oral, ophthalmic, or intravaginal use.

3 DOSAGE FORMS AND STRENGTHS

Ointment. Soft white (off white to yellow) paraffin based ointment with calcipotriene 0.005% and betamethasone dipropionate 0.064%.

4 CONTRAINDICATIONS

None.

5 WARNINGS AND PRECAUTIONS

5.1 Effects on Calcium Metabolism

Hypercalcemia and hypercalciuria have been reported with use of Taclonex®. If hypercalcemia or hypercalciuria develop, treatment should be discontinued until parameters of calcium metabolism have normalized. In the trials that included assessment of the effects of Taclonex® Ointment on calcium metabolism, such testing was done after 4 weeks of treatment. The effects of Taclonex® Ointment on calcium metabolism following treatment durations of longer than 4 weeks have not been evaluated.

5.2 Effects on Endocrine System

Systemic absorption of topical corticosteroids can produce reversible hypothalamic-pituitary-adrenal (HPA) axis suppression with the potential for clinical glucocorticosteroid insufficiency. This may occur during treatment or upon withdrawal of the topical corticosteroid.

HPA axis suppression has been observed with Taclonex® Ointment [see Clinical Pharmacology (12.2)]. The effects of Taclonex® Ointment on the HPA axis following treatment durations of longer than 4 weeks have not been adequately studied.

In a study of 32 subjects concomitantly treated with Taclonex® Scalp Topical Suspension on the scalp and Taclonex® Ointment on the body, adrenal suppression was identified in 5 of 32 subjects (15.6%) after 4 weeks of treatment [see CLINICAL PHARMACOLOGY Pharmacodynamics (12.2)].

Because of the potential for systemic absorption, use of topical corticosteroids may require that patients be periodically evaluated for HPA axis suppression. Factors that predispose a patient using a topical corticosteroid to HPA axis suppression include the use of more potent steroids, use over large surface areas, use over prolonged periods, use under occlusion, use on an altered skin barrier, and use in patients with liver failure.

An ACTH stimulation test may be helpful in evaluating patients for HPA axis suppression. If HPA axis suppression is documented, an attempt should be made to gradually withdraw the drug, to reduce the frequency of application, or to substitute a less potent steroid. Manifestations of adrenal insufficiency may require supplemental systemic corticosteroids. Recovery of HPA axis function is generally prompt and complete upon discontinuation of topical corticosteroids.

Cushing's syndrome, hyperglycemia, and unmasking of latent diabetes mellitus can also result from systemic absorption of topical corticosteroids.

Use of more than one corticosteroid-containing product at the same time may increase the total systemic corticosteroid exposure.

Pediatric patients may be more susceptible to systemic toxicity from use of topical corticosteroids [see Use in Specific Populations (8.4)].

5.3 Local Adverse Reactions with Topical Corticosteroids

Local adverse reactions may be more likely to occur with occlusive use, prolonged use or use of higher potency corticosteroids. Reactions may include atrophy, striae, telangiectasias, burning, itching, irritation, dryness, folliculitis, acneiform eruptions, hypopigmentation, perioral dermatitis, allergic contact dermatitis, secondary infection, and miliaria. Some local adverse reactions may be irreversible.

5.4 Allergic Contact Dermatitis with Topical Corticosteroids

Allergic contact dermatitis to any component of topical corticosteroids is usually diagnosed by a failure to heal rather than a clinical exacerbation. Clinical diagnosis of allergic contact dermatitis can be confirmed by patch testing.

5.5 Allergic Contact Dermatitis with Topical Calcipotriene

Allergic contact dermatitis has been observed with use of topical calcipotriene. Clinical diagnosis of allergic contact dermatitis can be confirmed by patch testing.

5.6 Concomitant Skin Infections

Concomitant skin infections should be treated with an appropriate antimicrobial agent. If the infection persists, Taclonex® Ointment should be discontinued until the infection has been adequately treated.

5.7 Skin Irritation

If irritation develops, treatment with Taclonex® Ointment should be discontinued and appropriate therapy instituted.

5.8 Unevaluated Uses

The safety and efficacy of Taclonex® Ointment in patients with known or suspected disorders of calcium metabolism have not been evaluated.

The safety and efficacy of Taclonex® Ointment in patients with erythrodermic, exfoliative, or pustular psoriasis have not been evaluated.

The safety and efficacy of Taclonex® Ointment in patients with severe renal insufficiency or severe hepatic disorders have not been evaluated.

5.9 Ultraviolet Light Exposure

Patients who apply Taclonex® Ointment to exposed skin should avoid excessive exposure to either natural or artificial sunlight, including tanning booths, sun lamps, etc. Physicians may wish to limit or avoid use of phototherapy in patients who use Taclonex® Ointment.

6 ADVERSE REACTIONS

Because clinical trials are conducted under widely varying conditions, adverse reaction rates observed in the clinical trials of a drug cannot be directly compared to rates in the clinical trials of another drug and may not reflect the rates observed in practice.

6.1 Clinical Study Experience

The data described below reflect exposure to Taclonex® Ointment in 2448 subjects, including 1992 exposed for 4 weeks, and 289 exposed for 8 weeks. Taclonex® Ointment was studied primarily in placebo- and active-controlled trials (N = 1176, and N = 1272, respectively). The population was 15-97 years old, 61% males and 39% females, mostly white (97%) and had a baseline disease severity ranging from mild to very severe. Most subjects received once daily application, and the median weekly dose was 24.5 g.

The percentage of subjects reporting at least one adverse event was 27.1% in the Taclonex® Ointment group, 33.0% in the calcipotriene group, 28.3% in the betamethasone group, and 33.4% in the vehicle group.

Table 1

Adverse Events Reported by ≥1% of Subjects by Preferred Term

 | Taclonex® Ointment N = 2448 | Calcipotriene N = 3197 | Betamethasone dipropionate N = 1164 | Vehicle N = 470
Any Adverse Event | 663 (27.1) | 1055 (33.0) | 329 (28.3) | 157 (33.4)
Preferred Term | # of subjects (%)
Pruritis | 75 (3.1) | 183 (5.7) | 38 (3.3) | 43 (9.1)
Headache | 69 (2.8) | 75 (2.3) | 44 (3.8) | 12 (2.6)
Nasopharyngitis | 56 (2.3) | 77 (2.4) | 34 (2.9) | 9 (1.9)
Psoriasis | 30 (1.2) | 47 (1.5) | 14 (1.2) | 5 (1.1)
Rash scaly | 30 (1.2) | 40 (1.3) | 0 (0.0) | 1 (0.2)
Influenza | 23 (0.9) | 34 (1.1) | 14 (1.2) | 6 (1.3)
Upper respiratory tract infection | 20 (0.8) | 19 (0.6) | 12 (1.0) | 3 (0.6)
Erythema | 15 (0.6) | 54 (1.7) | 3 (0.3) | 5 (1.1)
Application site pruritus | 13 (0.5) | 24 (0.8) | 10 (0.9) | 6 (1.3)
Skin irritation | 11 (0.4) | 60 (1.9) | 8 (0.7) | 5 (1.1)
Pain | 7 (0.3) | 12 (0.4) | 3 (0.3) | 5 (1.1)
Burning sensation | 6 (0.2) | 30 (0.9) | 3 (0.3) | 6 (1.3)

A lesional/perilesional adverse event was generally defined as an adverse event located ≤ 2 cm from the lesional border.
Table 2
Lesional/Perilesional Adverse Events Reported by ≥1% of Subjects

 | Taclonex® Ointment N = 2448 | Calcipotriene N = 3197 | Betamethasone dipropionate N = 1164 | Vehicle N = 470
Any Adverse Event | 213 (8.7) | 419 (13.1) | 85 (7.3) | 76 (16.2)
Preferred Term | # of subjects (%)
Pruritis | 69 (2.8) | 170 (5.3) | 31 (2.7) | 41 (8.7)
Rash scaly | 29 (1.2) | 38 (1.2) | 0 (0.0) | 0 (0.0)
Application site pruritus | 12 (0.5) | 24 (0.8) | 10 (0.9) | 6 (1.3)
Erythema | 9 (0.4) | 36 (1.1) | 2 (0.2) | 4 (0.9)
Skin irritation | 9 (0.4) | 51 (1.6) | 8 (0.7) | 5 (1.1)
Burning sensation | 6 (0.2) | 25 (0.8) | 3 (0.3) | 5 (1.1)

For subjects who reported lesional/perilesional adverse events, the median time to onset was 7 days for Taclonex® Ointment, 7 days for calcipotriene, 5 days for betamethasone dipropionate, and 3 days for vehicle.
Other less common reactions (less than 1% but more than 0.1%) were, in decreasing order of incidence, folliculitis, rash papular, rash pustular, and skin hypopigmentation. Skin atrophy, telangiectasia and skin hyperpigmentation were reported infrequently (0.1%).
In a separate study, subjects (N = 207) with at least moderate disease severity were given Taclonex® Ointment intermittently on an "as needed" basis for up to 52 weeks. The median use was 15.4 g per week. The effects of Taclonex® Ointment on calcium metabolism were not studied and the effects on the HPA axis were not adequately studied. The following adverse reactions were reported by 1% or more of the subjects: pruritus (7.2%), psoriasis (3.4%), skin atrophy (1.9%), folliculitis (1.4%), burning sensation (1.4%), skin depigmentation (1.4%), ecchymosis (1.0%), erythema (1.0%) and hand dermatitis (1.0%). One case of serious flare-up of psoriasis was reported.

6.2 Post-marketing Experience

The following adverse reactions associated with the use of Taclonex® Ointment have been identified post-approval: pustular psoriasis and rebound effect.

Because these reactions are reported voluntarily from a population of uncertain size, it is not always possible to reliably estimate their frequency or establish a causal relationship to drug exposure.

8 USE IN SPECIFIC POPULATIONS

8.1 Pregnancy

Teratogenic Effects: Pregnancy Category C

There are no adequate and well-controlled studies in pregnant women. Pregnant women were excluded from the clinical studies conducted with Taclonex® Ointment. Taclonex® Ointment should be used during pregnancy only if the potential benefit to the patient justifies the potential risk to the fetus. Animal reproduction studies have not been conducted with Taclonex® Ointment. Taclonex® Ointment contains calcipotriene that has been shown to be fetotoxic and betamethasone dipropionate that has been shown to be teratogenic in animals when given systemically.

Teratogenicity studies with calcipotriene were performed by the oral route in rats and rabbits. In rabbits, increased maternal and fetal toxicity were noted at a dosage of 12 mcg/kg/day (144 mcg/m^2/day); a dosage of 36 mcg/kg/day (432 mcg/m^2/day) resulted in a significant increase in the incidence of incomplete ossification of the pubic bones and forelimb phalanges of fetuses. In a rat study, a dosage of 54 mcg/kg/day (324 mcg/m^2/day) resulted in a significantly increased incidence of skeletal abnormalities (enlarged fontanelles and extra ribs). The enlarged fontanelles are most likely due to the effect of calcipotriene upon calcium metabolism. The estimated maternal and fetal no-adverse effect levels (NOAEL) in the rat (108 mcg/m^2/day) and rabbit (48 mcg/m^2/day) derived from oral studies are lower than the estimated maximum topical dose of calcipotriene in man (460 mcg/m^2/day).

Corticosteroids are generally teratogenic in laboratory animals when administered systemically at relatively low dosage levels.
Betamethasone dipropionate has been shown to be teratogenic in mice and rabbits when given by the subcutaneous route at doses of 156 mcg/kg/day (468 mcg/m^2/day) and 2.5 mcg/kg/day (30 mcg/m^2/day), respectively. Those dose levels are lower than the estimated maximum topical dose in man (about 5950 mcg/m^2/day). The abnormalities observed included umbilical hernia, exencephaly and cleft palate.
Two oral peri- and post-natal development studies were conducted with rats:
Pregnant Wistar rats were dosed daily with calcipotriene at exposures of 0, 6, 18 or 54 mcg/kg/day from gestation day 15 through day 20 postpartum. No remarkable effects were observed on any parameter, including survival, behavior, body weight, litter parameters, or the ability to nurse or rear pups.
Betamethasone dipropionate was evaluated for effects when orally administered to pregnant rats from gestation day 6 through day 20 postpartum at dosages of 0, 100, 300, and 1000 mcg/kg/day. Mean maternal body weight was significantly reduced on gestation day 20 in animals dosed at 300 and 1000 mcg/kg/day. The mean duration of gestation was slightly, but statistically significantly, increased at 100, 300, and 1000 mcg/kg/day. The mean percentage of pups that survived to day 4 was reduced in relation to dosage. On lactation day 5, the percentage of pups with a reflex to right themselves when placed on their back was significantly reduced at 1000 mcg/kg/day. No effects on the ability of pups to learn were observed, and the ability of the offspring of treated rats to reproduce was not affected.

8.3 Nursing Mothers

Systemically administered corticosteroids appear in human milk and could suppress growth, interfere with endogenous corticosteroid production, or cause other untoward effects.

It is not known whether topically administered calcipotriene or corticosteroids could result in sufficient systemic absorption to produce detectable quantities in human milk.

Because many drugs are excreted in human milk, caution should be exercised when Taclonex® Ointment is administered to a nursing woman.

8.4 Pediatric Use

Safety and effectiveness of the use of Taclonex® Ointment in pediatric patients have not been studied. Because of a higher ratio of skin surface area to body mass, children under the age of 12 years may be at particular risk of systemic adverse effects when they are treated with topical medication [see Warnings and Precautions (5.2)].

HPA axis suppression, Cushing's syndrome, linear growth retardation, delayed weight gain, and intracranial hypertension have been reported in children receiving topical corticosteroids. Manifestations of adrenal suppression in children include low plasma cortisol levels and absence of response to ACTH stimulation. Manifestations of intracranial hypertension include bulging fontanelles, headaches, and bilateral papilledema.

8.5 Geriatric Use

Of the total number of subjects in the clinical studies of Taclonex® Ointment, approximately 14% were 65 years and older and approximately 3% were 75 years and over.

No overall differences in safety or effectiveness of Taclonex® Ointment were observed between these subjects and younger subjects. All other reported clinical experience has not identified any differences in response between elderly and younger patients.

10 OVERDOSAGE

Topically applied Taclonex® Ointment can be absorbed in sufficient amounts to produce systemic effects [see Warnings and Precautions (5.1, 5.2)].

11 DESCRIPTION

Taclonex® Ointment contains calcipotriene hydrate and betamethasone dipropionate. It is intended for topical use.

Calcipotriene hydrate is a synthetic vitamin D3 analogue.

Chemically, calcipotriene hydrate is (5Z,7E,22E,24S)-24-cyclopropyl-9,10-secochola-5,7,10(19),22-tetraene-1(alpha),3(beta),24-triol,hydrate, with the empirical formula C27H40O3H2O, a molecular weight of 430.6, and the following structural formula:

Calcipotriene hydrate is a white to almost white crystalline compound.

Betamethasone dipropionate is a synthetic corticosteroid.

Betamethasone dipropionate has the chemical name 9-fluoro-11(beta),17,21-trihydroxy-16(beta)-methylpregna-1,4-diene-3,20-dione17,21-dipropionate, with the empirical formula C28H37FO7, a molecular weight of 504.6, and the following structural formula:

Betamethasone dipropionate is a white to almost white odorless powder.

Each gram of Taclonex® Ointment contains 52.18 mcg of calcipotriene hydrate (equivalent to 50 mcg of calcipotriene) and 0.643 mg of betamethasone dipropionate (equivalent to 0.5 mg of betamethasone) in an ointment base of mineral oil, PPG-15 stearyl ether, dl-alpha tocopherol and white petrolatum.

12 CLINICAL PHARMACOLOGY

12.1 Mechanism of Action

Taclonex® Ointment combines the pharmacological effects of calcipotriene hydrate as a synthetic vitamin D3 analogue and betamethasone dipropionate as a synthetic corticosteroid. However, while their pharmacologic and clinical effects are known, the exact mechanisms of their actions in psoriasis vulgaris are unknown.

12.2 Pharmacodynamics

Vasoconstriction:

In a vasoconstrictor study, the skin blanching response of Taclonex® Ointment was consistent with that of a potent corticosteroid.

Hypothalamic-Pituitary-Adrenal (HPA) Axis Suppression:

Taclonex® Ointment was applied once daily for 4 weeks to adult subjects (N = 12) with psoriasis vulgaris to study its effects on the hypothalamic-pituitary-adrenal (HPA) axis. Of eleven subjects tested, none demonstrated adrenal suppression as indicated by a 30-minute post-stimulation cortisol level ≤ 18 mcg/dL.

However in another clinical study of Taclonex® Ointment, one subject (N = 19) demonstrated adrenal suppression.

HPA axis suppression was evaluated in adult subjects (N=32) with extenisve psoriasis involving at least 30% of the scalp and, in total, 15-30% of the body surface area. Treatment consited of once daily application of Talconex Scalp® Topical Suspension on the scalp in combination with Taclonex® Ointment on the body. Adrenal suppression as indicated by a 30-minutes post-stimulation cortisol level less than or equal to 18 mcg/dL was observed in 5 of 32 subjects (15.6%) after 4 weeks of treatment as per the recommended duration of use (see Dosage and Administration (2.1).

Effects on Calcium Metabolism

In the combination use study described above, the effects of once daily application of Taclonex® Ointment on the body in combination with Taclonex Scalp® Topical Suspension on the scalp on calcium metabolism were also examined. Elevated urinary calcium levels outside the normal range were observed in 1 of 35 subjects (2.9%) after 4 weeks of treatment.

12.3 Pharmacokinetics

Absorption

The systemic effect of Taclonex® Ointment in extensive psoriasis was investigated in the study described above. In this study, the serum levels of calcipotriene and betamethasone dipropionate and their major metabolites were measured after 4 weeks (maximum recommended duration of treatment) and also after 8 weeks of once daily application of Taclonex® Ointment on the body in combination with Taclonex Scalp® Topical Suspension on the scalp. Both calcipotriene and betamethasone dipropionate were below the lower limit of quantification in all serum samples of the 34 subjects evaluated. However, one major metabolite of calcipotriene (MC1080) was quantifiable in 10 of 34 (29.4%) subjects at week 4 and in five of 12 (41.7%) subjects at week 8. The major metabolite of betamethasone dipropionate, betamethasone 17-propionate (B17P) was also quantifiable in 19 of 34 (55.9%) subjects at week 4 and seven of 12 (58.3%) subjects at week 8. The serum concentrations for MC1080 ranged from 20-75 pg/mL. The clinical significance of this finding is unknown.

Metabolism

Calcipotriene:
Calcipotriene metabolism following systemic uptake is rapid and occurs in the liver. The primary metabolites of calcipotriene are less potent than the parent compound.

Calcipotriene is metabolized to MC1046 (the alpha,beta-unsaturated ketone analogue of calcipotriene), which is metabolized further to MC1080 (a saturated ketone analogue). MC1080 is the major metabolite in plasma. MC1080 is slowly metabolized to calcitroic acid.

Betamethasone dipropionate:
Betamethasone dipropionate is metabolized to betamethasone 17-propionate and betamethasone, including the 6beta-hydroxy derivatives of those compounds by hydrolysis. Betamethasone 17-propionate (B17P) is the primary metabolite.

13 NONCLINICAL TOXICOLOGY

13.1 Carcinogenesis, Mutagenesis, Impairment of Fertility

When calcipotriene was applied topically to mice for up to 24 months at dosages of 3, 10 and 30 mcg/kg/day (corresponding to 9, 30 and 90 mcg/m^2/day), no significant changes in tumor incidence were observed when compared to control.

In a study in which albino hairless mice were exposed to both ultra-violet radiation (UVR) and topically applied calcipotriene, a reduction in the time required for UVR to induce the formation of skin tumors was observed (statistically significant in males only), suggesting that calcipotriene may enhance the effect of UVR to induce skin tumors.

Long-term animal studies have not been performed to evaluate the carcinogenic potential of betamethasone dipropionate.

Calcipotriene did not elicit any genotoxic effects in the Ames mutagenicity assay, the mouse lymphoma TK locus assay, the human lymphocyte chromosome aberration test, or the mouse micronucleus test.

Betamethasone dipropionate did not elicit any genotoxic effects in the Ames mutagenicity assay, the mouse lymphoma TK locus assay, or in the rat micronucleus test.

Studies in rats with oral doses of up to 54 mcg/kg/day (324 mcg/m^2/day) of calcipotriene indicated no impairment of fertility or general reproductive performance.

Studies in male rats at oral doses of up to 200 mcg/kg/day (1200 mcg/m^2/day), and in female rats at oral doses of up to 1000 mcg/kg/day (6000 mcg/m^2/day), of betamethasone dipropionate indicated no impairment of fertility.

14 CLINICAL STUDIES

14.1 Controlled Clinical Studies

In an international, multi-center, double-blind, vehicle- and active-controlled, parallel-group study, 1603 subjects with mild to very severe psoriasis vulgaris on trunk and limbs were treated once daily for 4 weeks. Subjects were randomized to one of four treatment arms: Taclonex® Ointment, calcipotriene hydrate 50 mcg/g in the same vehicle, betamethasone dipropionate 0.64 mg/g in the same vehicle, and vehicle alone. The mean age of the subjects was 48.4 years and 60.5% were male. Most subjects had disease of moderate severity at baseline.

Efficacy was assessed as the proportion of subjects with absent or very mild disease according to the Investigator's Global Assessment of Disease Severity at end of treatment (4 weeks). "Absent" disease was defined as no evidence of redness, thickness, or scaling. "Very mild disease" was defined as controlled disease, but not entirely cleared: lesions with some discoloration with absolutely minimal thickness, i.e. the edges to the lesions(s) could just be felt. Table 3 contains the response rates for this trial.

Table 3

Percentage of Subjects with Absent or Very Mild Disease According to the Investigator's Global Assessment of Disease Severity at End of Treatment (4 weeks).*

 | Taclonex® Ointment N = 490 | Calcipotriene N = 480 | Betamethasone dipropionate N = 476 | Vehicle N = 157
Absent or very mild disease | 48.0% | 16.5% | 26.3% | 7.6%

*Subjects with mild disease at baseline were required to have "Absent" disease to be considered a success.
In addition to the pivotal study (N = 490), four randomized, double-blind, vehicle- or active-controlled, parallel-group studies were conducted and provided supportive evidence of efficacy. These studies included a total of 1058 subjects treated with Taclonex® Ointment once daily for up to 4 weeks.

16 HOW SUPPLIED/STORAGE AND HANDLING

16.1 How Supplied

Taclonex® Ointment is available in collapsible tubes of:

60 gram (NDC 54868-5680-0)

16.2 Storage

Store Taclonex® Ointment between 20 - 25° C (68 - 77° F); excursions permitted between 15 - 30° C (59 - 86° F).

16.3 Handling

Keep out of reach of children.

17 PATIENT COUNSELING INFORMATION

[See FDA-Approved Patient Labeling (17.5)]

This information is intended to aid in the safe and effective use of this medication. It is not a disclosure of all possible adverse or intended effects.

Patients using Taclonex® Ointment should receive the following information and instructions.

17.1 Instructions for Use

This medication is to be used as directed by the physician. It is for external use only. Avoid contact with the face or eyes. As with any topical medication, patients should wash hands after application. This medication should not be used for any disorder other than that for which it has been prescribed. The treated skin area should not be bandaged or otherwise covered as to be occlusive, unless directed by the physician.

17.2 Adverse Reactions

Patients should report any signs of adverse reactions to their physician.

17.3 Concomitant Use of Other Corticosteroids

Other products containing calcipotriene or a corticosteroid should not be used with Taclonex® Ointment without first talking to the physician.

17.4 Excessive Exposure to Light

Patients who apply Taclonex® Ointment to exposed portions of the body should avoid excessive exposure to either natural or artificial sunlight (including tanning booths, sun lamps, etc.). Physicians may wish to limit or avoid use of phototherapy in patients who use Taclonex® Ointment.

17.5 FDA-Approved Patient Labeling

Patient Information
Taclonex® Ointment (pronounced TAK-lo-NEKS)
(calcipotriene 0.005% and betamethasone dipropionate 0.064%)
Read the Patient Information that comes with Taclonex® Ointment before you start using it and each time you refill your prescription. There may be new information. This leaflet does not take the place of talking with your doctor about your condition or treatment.
Important information: Taclonex® Ointment is for use on the skin only (topical use only). Do not use Taclonex® Ointment on the face, under arms or on groin area. Do not swallow Taclonex® Ointment. Another product, Taclonex Scalp® Topical Suspension contains the same medicine that is in Taclonex® Ointment and is used to treat psoriasis vulgaris on the scalp. If you use both medicines to treat your psoriasis vulgaris, be sure to follow your doctor’s directions carefully so that you do not use too much of one or both of these medications.
What is Taclonex® Ointment?
Taclonex® Ointment is a prescription medicine that is for use on the skin only (a topical medicine). Taclonex® Ointment is used to treat psoriasis vulgaris in adults 18 years of age and older.
Taclonex® Ointment is not recommended for use in children. Taclonex® Ointment has not been studied in patients under the age of 18.
Who should not use Taclonex® Ointment?
Do not use Taclonex® Ointment if you:
• have a calcium metabolism disorder
• have one of the following types of psoriasis:
o erythrodermic psoriasis
o exfoliative psoriasis
o pustular psoriasis
• have severe kidney or liver disease
• are allergic to anything in Taclonex® Ointment. See the end of this leaflet for a complete list of ingredients.
What should I tell my doctor before using Taclonex® Ointment?
Tell your doctor about all of your health conditions, including if you:
• have a skin infection. Your skin infection should be treated before starting Taclonex® Ointment.
• have thin-skin (atrophy) at the site to be treated. You should not use Taclonex® Ointment.
• are getting phototherapy treatments (light therapy) for your psoriasis.
• are pregnant or planning to become pregnant. It is not known if Taclonex® Ointment can harm your unborn baby. You and your doctor will have to decide if Taclonex® Ointment is right for you while pregnant.
• are breastfeeding. It is not known if Taclonex® Ointment passes into your milk and if it can harm your baby.
Tell your doctor about all the medicines you take, including prescription, and nonprescription medicines, vitamins and herbal supplements. Taclonex® Ointment and some other medicines can interact with each other. Especially tell your doctor if you use:
• other corticosteroid medicines
• other medicines for your psoriasis
How should I use Taclonex® Ointment?
• Use Taclonex® Ointment exactly as prescribed by your doctor.
• Do not use more than the maximum recommended weekly amount of 100 grams of Taclonex® Ointment.
• Apply Taclonex® Ointment once a day to the areas of your skin affected by psoriasis. Gently rub Taclonex® Ointment into your affected skin areas.
• Only use Taclonex® Ointment as directed by your doctor. Taclonex® Ointment is recommended for up to 4 weeks of treatment. Do not use Taclonex® Ointment for more than 4 weeks unless prescribed by your doctor.
• Do not use Taclonex® Ointment on the face, under arms or on groin area. If you accidentally get Taclonex® Ointment on the face or in the eyes wash the area with water right away.
• If you forget to use Taclonex® Ointment, use it as soon as you remember. Then go on as before.
• Wash your hands well after applying Taclonex® Ointment.
Using Taclonex® Ointment:
Do not bandage or tightly cover the treated skin area.
Remove the cap and check that the aluminum seal covers the tube before the first use. To break the seal, turn the cap over and punch through the seal.
What should I avoid while using Taclonex® Ointment?
Avoid spending a long time in the sunlight. Avoid tanning booths and sunlamps. Use sunscreen if you have to be in the sunlight. Talk to your doctor if you get a sunburn.
What are the possible side effects of Taclonex® Ointment?
The most common side effects are:
• itching
• rash
Other less common side effects with Taclonex® Ointment include:
• redness of the skin
• skin irritation
• skin burning
• inflamed hair pores (folliculitis)
• change of skin color (at the site of application)
• rash with pus-filled papules
• thinning of the skin (atrophy)
• swollen fine blood vessels (this makes your skin appear red at the site of application)
Taclonex® Ointment may cause serious side effects. Serious side effects are more likely to happen if you use too much Taclonex® Ointment, use it for too long, or use it with other topical medicines that contain corticosteroids, calcipotriene, or certain other ingredients. Check with your doctor before using other topical medicines. Taclonex® Ointment can pass through your skin. Serious side effects may include:
• too much calcium in your blood or urine
• adrenal gland problems
Your doctor may do special blood and urine tests to check your calcium levels and adrenal gland function while you are using Taclonex® Ointment.
Call your doctor about any side effect that bothers you or that does not go away.
These are not all of the side effects with Taclonex® Ointment. Ask your doctor or pharmacist for more information.
How should I store Taclonex® Ointment?
• Store Taclonex® Ointment between 68 - 77° F (20 - 25° C); excursions permitted between 59 - 86° F (15 - 30° C).
• Make sure the cap on the tube is tightly closed.
• Taclonex® Ointment has an expiration date (exp.) marked on the tube. Do not use the ointment after this date.
• Keep Taclonex® Ointment and all medicines out of the reach of children and pets.
General information about Taclonex® Ointment
Medicines are sometimes prescribed for conditions that are not mentioned in patient information leaflets. Do not use Taclonex® Ointment for a condition for which it was not prescribed. Do not give Taclonex® Ointment to other people, even if they have the same symptoms you have. It may harm them.
This leaflet summarizes the most important information about Taclonex® Ointment. If you would like more information, talk with your doctor. You can ask your doctor or pharmacist for information about Taclonex® Ointment that is written for health professionals.
What are the ingredients in Taclonex® Ointment?
Active ingredients: calcipotriene hydrate, betamethasone dipropionate.
Inactive ingredients: mineral oil, PPG-15 stearyl ether, dl-alpha tocopherol, white petrolatum.

Manufactured by:
LEO Laboratories Ltd. (LEO Pharma)
Dublin, Ireland
Distributed by:
LEO Pharma Inc.
1 Sylvan Way, Parsippany, NJ 07054 USA
1-877-494-4536
U.S. Patent Nos.: RE39,706 E and 6,753,013.
024598-01
024599-01
Revised: 11/2010

Additional barcode labeling by:
Physicians Total Care, Inc.
Tulsa, Oklahoma 74146

PRINCIPAL DISPLAY PANEL

NDC 54868-5680-0

TACLONEX® (calcipotriene 0.005% and betamethasone dipropionate 0.064%) Ointment
Rx Only
For Topical Use Only
Net Wt. 60 g

Each gram contains 52.18 mcg of calcipotriene hydrate (equivalent to 50 mcg of calcipotriene) and 0.643 mg of betamethasone dipropionate (equivalent to 0.5 mcg of betamethasone) in an ointment base of mineral oil, PPG-15 stearyl ether, dl-alpha tocopherol and white petrolatum.

Store Taclonex Ointment between 20 - 25° C (68 - 77° F); excursions permitted between 15 - 30° C (59 - 86° F).
Keep out of reach of children.
Usual Dosage: Apply once daily, or as directed by physician. See Insert for complete information.